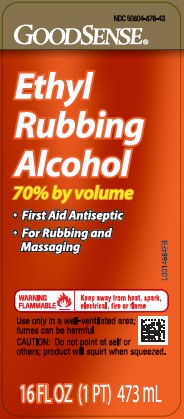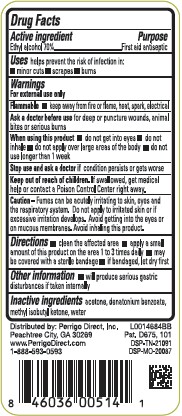 DRUG LABEL: Rubbing
NDC: 50804-876 | Form: LIQUID
Manufacturer: Perrigo Direct, Inc
Category: otc | Type: HUMAN OTC DRUG LABEL
Date: 20260219

ACTIVE INGREDIENTS: ALCOHOL 70 mL/100 mL
INACTIVE INGREDIENTS: ACETONE; DENATONIUM BENZOATE; METHYL ISOBUTYL KETONE; WATER

Good Sense 876.002/876AC
Ethyl Rubbing Alcohol 70%

Active Ingredient

Ethyl alcohol 70%

Purpose

First aid antiseptic

Uses

first aid to help prevent the risk of infection in:

- minor cuts
- scrapes
- burns

Warnings

For external use only

Flammable. Keep away from fire or flame, heat, spark, electrical.

Ask a doctor before use

for deep or puncture wounds, animal bites or serious burns

When using this product

- do not get into eyes
- do not inhale
- do not apply over large areas of the body
- do not use longer than 1 week

Stop use and ask a doctor if

condition persists or gets worse

Keep out of reach of children.

If swallowed, get medical help or contact a Poison Control Center right away.

Caution

Fumes can be acutely irritating to skin, eyes and the respiratory system. Do not apply to irritated skin or if excessive irritation develops. Avoid getting into the eyes or on mucous membranes. Avoid inhaling this product.

Directions

- clean the affected area
- apply a small amount of this product on the affected area 1 to 3 times daily
- may be covered with a sterile bandage
- if bandaged, let dry first

other information

will produce serious gastric disturbances if taken internally

Inactive ingredients

acetone, denatonium benzoate, methyl isobutyl ketone, water

ADVERSE REACTION

Distributed by: Perrigo Direct, Inc.

Peachtree City, GA 30269

www.PerrigoDirect.com

1-888-593-0593

Pat. D675, 101

DSP-TN-21091

DSP-MO-20087

principal display panel

NDC 50804-876-43

Good Sense®

Ethyl

Rubbing

Alcohol

70% by volume

- First Aid Antiseptic
- For Rubbing and Massaging

WARNING FLAMMABLE - Keep away from heat, spark, electrical, fire or flame

Use only in a well ventilated area; fumes can be harmful

CAUTION: Do not point at self or others; product will squirt when squeezed.

16 FL OZ (1 PT) 473 mL